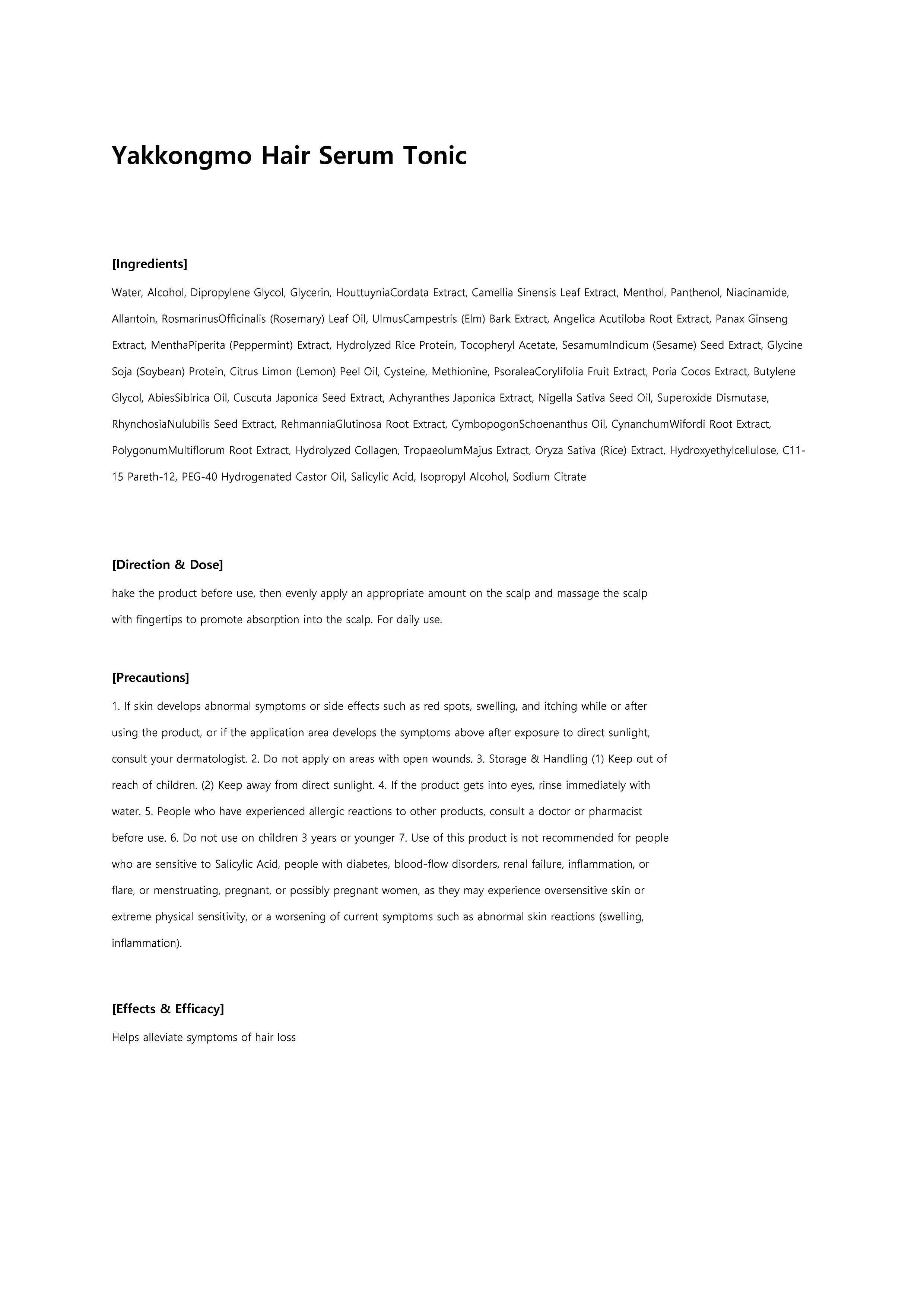 DRUG LABEL: Yakkongmo hair serum tonic
NDC: 73540-002 | Form: LIQUID
Manufacturer: BOBSNU CO., LTD.
Category: otc | Type: HUMAN OTC DRUG LABEL
Date: 20200222

ACTIVE INGREDIENTS: LEVOMENTHOL 0.3 g/100 mL; SALICYLIC ACID 0.25 g/100 mL; DEXPANTHENOL 0.2 g/100 mL
INACTIVE INGREDIENTS: WATER

ACTIVE INGREDIENT

L-menthol, dexpanthenol, salicylic acid

INACTIVE INGREDIENT

Water, Alcohol, Dipropylene Glycol, Glycerin, HouttuyniaCordata Extract, Camellia Sinensis Leaf Extract, Menthol, Panthenol, Niacinamide, Allantoin, RosmarinusOfficinalis (Rosemary) Leaf Oil, UlmusCampestris (Elm) Bark Extract, Angelica Acutiloba Root Extract, Panax Ginseng Extract, MenthaPiperita (Peppermint) Extract, Hydrolyzed Rice Protein, Tocopheryl Acetate, SesamumIndicum (Sesame) Seed Extract, Glycine Soja (Soybean) Protein, Citrus Limon (Lemon) Peel Oil, Cysteine, Methionine, PsoraleaCorylifolia Fruit Extract, Poria Cocos Extract, Butylene Glycol, AbiesSibirica Oil, Cuscuta Japonica Seed Extract, Achyranthes Japonica Extract, Nigella Sativa Seed Oil, Superoxide Dismutase, RhynchosiaNulubilis Seed Extract, RehmanniaGlutinosa Root Extract, CymbopogonSchoenanthus Oil, CynanchumWifordi Root Extract, PolygonumMultiflorum Root Extract, Hydrolyzed Collagen, TropaeolumMajus Extract, Oryza Sativa (Rice) Extract, Hydroxyethylcellulose, C11-15 Pareth-12, PEG-40 Hydrogenated Castor Oil, Salicylic Acid, Isopropyl Alcohol, Sodium Citrate

PURPOSE

Helps alleviate symptoms of hair loss

WARNINGS

1. If skin develops abnormal symptoms or side effects such as red spots, swelling, and itching while or after using the product, or if the application area develops the symptoms above after exposure to direct sunlight, consult your dermatologist.

2. Do not apply on areas with open wounds.

3. Storage & Handling (1) Keep out of reach of children. (2) Keep away from direct sunlight.

4. If the product gets into eyes, rinse immediately with water.

5. People who have experienced allergic reactions to other products, consult a doctor or pharmacist before use.

6. Do not use on children 3 years or younger

7. Use of this product is not recommended for people who are sensitive to Salicylic Acid, people with diabetes, blood-flow disorders, renal failure, inflammation, or flare, or menstruating, pregnant, or possibly pregnant women, as they may experience oversensitive skin or extreme physical sensitivity, or a worsening of current symptoms such as abnormal skin reactions (swelling, inflammation).

Keep Out of Reach of Children

Directions

hake the product before use, then evenly apply an appropriate amount on the scalp and massage the scalp with fingertips to promote absorption into the scalp. For daily use.

INDICATIONS AND USAGE

Helps alleviate symptoms of hair loss